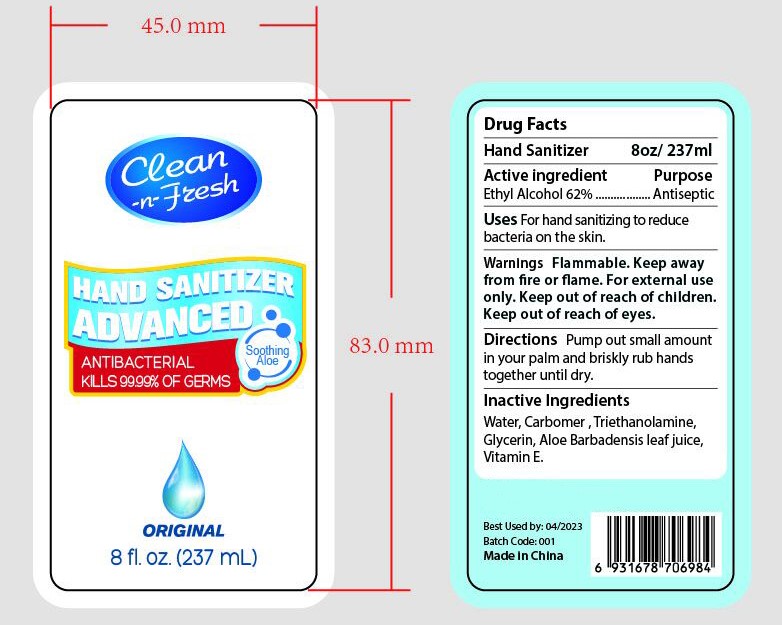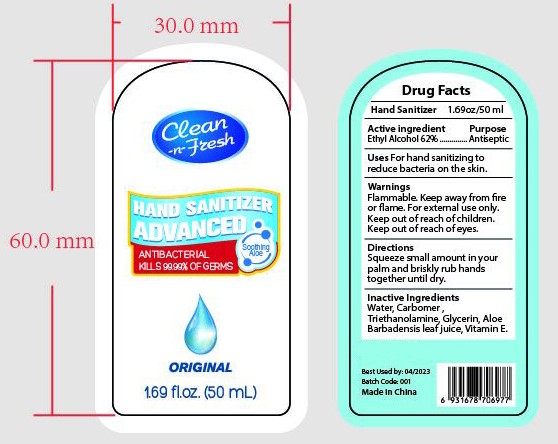 DRUG LABEL: HAND SANITIZER
NDC: 47993-219 | Form: GEL
Manufacturer: NINGBO JIANGBEI OCEAN STAR TRADING CO.,LTD
Category: otc | Type: HUMAN OTC DRUG LABEL
Date: 20201103

ACTIVE INGREDIENTS: ALCOHOL 62 g/112 mL
INACTIVE INGREDIENTS: CARBOMER 940 12 g/112 mL; TRIETHANOLAMINE BENZOATE 3 g/112 mL; TOCOPHEROL 0.1 g/112 mL; ALOE VERA LEAF 1 g/112 mL; WATER 19.9 g/112 mL; GLYCERIN 2 g/112 mL

47993-219

Active ingredients

Ethyl Alcohol 62%

PURPOSE

Antiseptic

Warnings:

Flammable.Keep away from fire or flame.For external use only.Keep out of reach of children.Keep out of reach of eyes.

Uses：

For hand sanitizing to reduce bacteria on the skin.

Directions:

Pump out small amount in your palm and briskly rub hands together until dry.

Keep out of reach of children.

Inactive Ingredients:

Water,Carbomer,Triethanolamine,Glycerin,Aloe Barbadensis leaf juice,Vitamin E